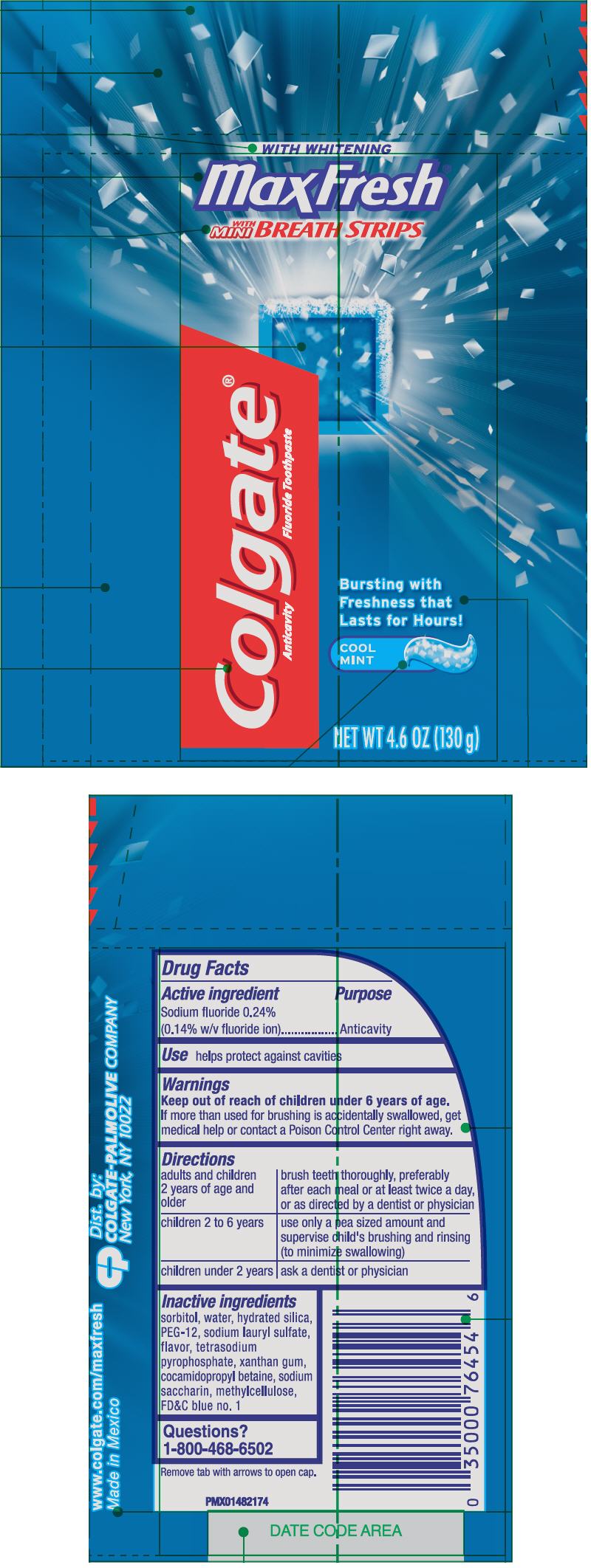 DRUG LABEL: Colgate Max Fresh Cool Mint
NDC: 35000-947 | Form: GEL, DENTIFRICE
Manufacturer: Colgate-Palmolive Company
Category: otc | Type: HUMAN OTC DRUG LABEL
Date: 20191211

ACTIVE INGREDIENTS: SODIUM FLUORIDE 1.1 mg/1 g
INACTIVE INGREDIENTS: SORBITOL 665.38 mg/1 g; WATER; HYDRATED SILICA; POLYETHYLENE GLYCOL 600; SODIUM LAURYL SULFATE; SODIUM PYROPHOSPHATE; XANTHAN GUM; COCAMIDOPROPYL BETAINE; SACCHARIN SODIUM; METHYLCELLULOSE (100 MPA.S); FD&C BLUE NO. 1

Colgate® Max Fresh® Cool Mint 4.6oz 2in1 Fluoride Toothpaste

Drug Facts

Active ingredient

Sodium fluoride 0.24% (0.14% w/v fluoride ion)

Purpose

Anticavity

Use

helps protect against cavities

Warnings

Keep out of reach of children under 6 years of age. If more than used for brushing is accidentally swallowed, get medical help or contact a Poison Control Center right away.

Directions

adults and children 2 years of age and older | brush teeth thoroughly, preferably after each meal or at least twice a day, or as directed by a dentist or physician
children 2 to 6 years | use only a pea sized amount and supervise child's brushing and rinsing (to minimize swallowing)
children under 2 years | ask a dentist or physician

Inactive ingredients

sorbitol, water, hydrated silica, PEG-12, sodium lauryl sulfate, flavor, tetrasodium pyrophosphate, xanthan gum, cocamidopropyl betaine, sodium saccharin, methylcellulose, FD&C blue no. 1

Questions?

1-800-468-6502

Dist by:
COLGATE-PALMOLIVE COMPANY
New York, NY 10022

PRINCIPAL DISPLAY PANEL - 130 g Bottle Label

WITH WHITENING

MaxFresh®

WITH
MINI
BREATH STRIPS

Colgate®
Anticavity Fluoride Toothpaste

Bursting with
Freshness that
Lasts for Hours!

COOL
MINT

NET WT 4.6 OZ (130 g)